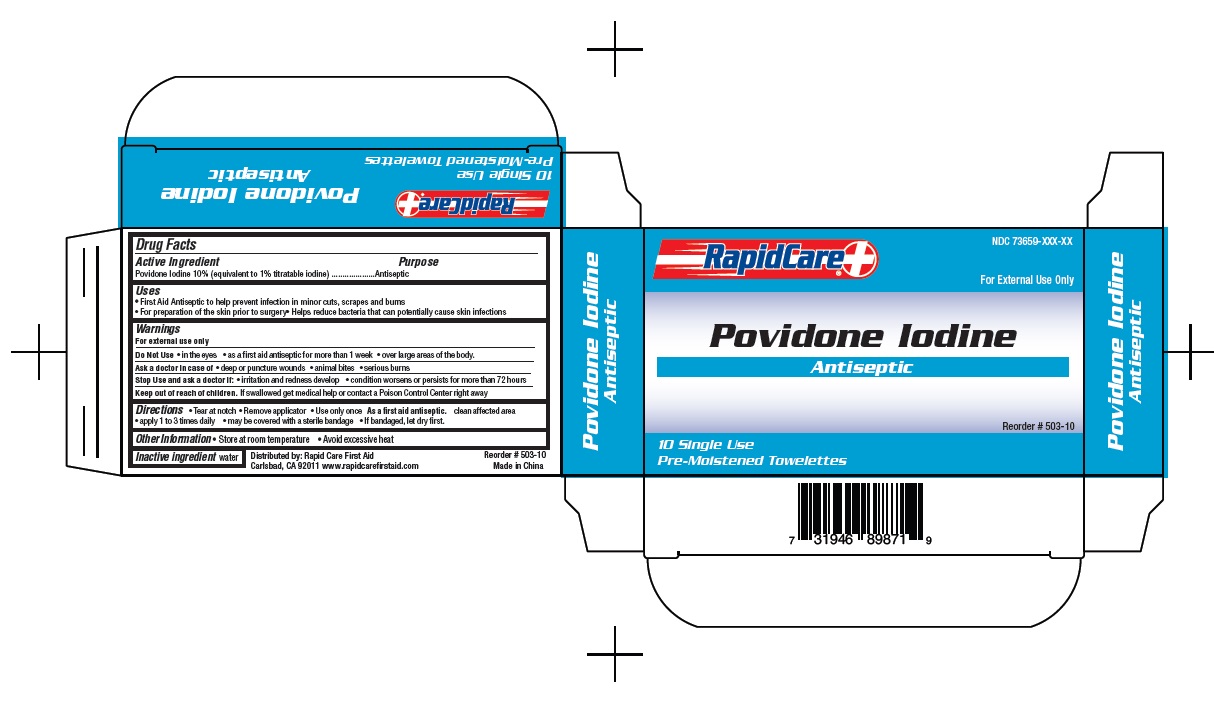 DRUG LABEL: Povidone Iodine
NDC: 73659-008 | Form: SWAB
Manufacturer: Rapid Care, Inc
Category: otc | Type: HUMAN OTC DRUG LABEL
Date: 20211014

ACTIVE INGREDIENTS: POVIDONE-IODINE 10 mg/1 1
INACTIVE INGREDIENTS: WATER

RapidCare - Povidone Iodine - 10pc

Active Ingredients

Povidone Iodine 10% (equivalent to 1% titratable iodine)

Purpose

Antiseptic

Uses

- First Aid Antiseptic to help prevent infection in minor cuts, scrapes or burns
- For preparation of the skin prior to surgery
- Helps reduce bacteria that can potentially cause skin infections

Warnings

For external use only

Do Not Use

- in the eyes
- as a first aid antiseptic for more that 1 week
- over large areas of the body

Ask a doctor in case of

- deep or puncture wounds
- animal bites
- serious burns

Stop use and ask a doctor if

- if irritation and redness develop.
- condition worsens or persists for more thatn 72 hours.

Keep out of reach of children.

If swallowed get medical help or contact a Poison Control Center right away

Directions

- Tear at notch
- Remove applicator
- Use only once

As a first aid antiseptic. clean affected area

- apply 1 to 3 times daily
- may be covered with a sterile bandage
- if bandage, let dry first

Other Information

- Store at room temperature
- Avoid excessive heat

Inactive ingredient

water